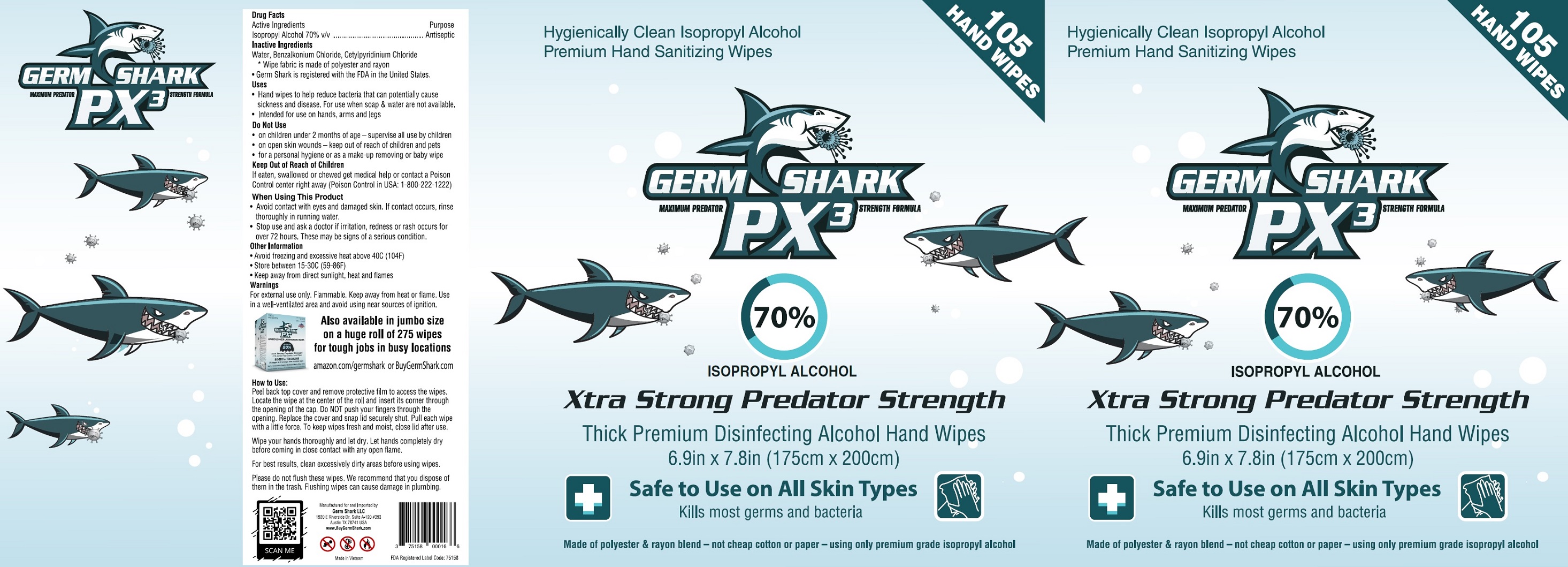 DRUG LABEL: Germ Shark PX3 Thick Premium Disinfecting Alcohol Hand Wipes 70 Isopropyl Alcohol
NDC: 75158-007 | Form: CLOTH
Manufacturer: Germ Shark, LLC
Category: otc | Type: HUMAN OTC DRUG LABEL
Date: 20201014

ACTIVE INGREDIENTS: ISOPROPYL ALCOHOL 0.7 mL/1 mL
INACTIVE INGREDIENTS: WATER; BENZALKONIUM CHLORIDE; CETYLPYRIDINIUM CHLORIDE

Germ Shark PX3 Thick Premium Disinfecting Alcohol Hand Wipes 70% Isopropyl Alcohol

Active Ingredients

Isopropyl Alcohol 70% v/v

Purpose

Antiseptic

Inactive Ingredients

Water, Benzalkonium Chloride, Cetylpyridinium Chloride

* Wipe fabric is made of polyester and rayon

- Germ Shark is registered with the FDA in the United States.

Uses

- Hand wipes to help reduce bacteria that can potentially cause sickness and disease. For use when soap & water are not available.
- Intended for use on hands, arms and legs

Warnings

For external use only. Flammable. Keep away from heat or flame. Use in a well-ventilated area and avoid using near sources of ignition.

Do Not Use

- on children under 2 months of age - supervise all use by children
- on open skin wounds - keep out of reach of children and pets
- for a personal hygiene or as a make-up removing or baby wipe

Keep Out of Reach of Children

If eaten, swallowed or chewed get medical help or contact a Poison Control center right away (Poison Control in USA: 1-800-222-1222)

When Using This Product

- Avoid contact with eyes and damaged skin, If contact, occurs, rinse thoroughly in running water.

Stop use and ask a doctor

if irritation, redness or rash occurs for over 72 hours, These may be signs of a serious condition.

Other Information

- Avoid freezing and excessive heat above 40C (104F)
- Store between 15-30C (59-86F)
- Keep away from direct sunlight, heat and flames

How to Use:

Peel back top cover and remove protective film to access the wipes. Locate the wipe at the center of the roll and insert its corner through the opening of the cap. Do NOT push your fingers through the opening. Replace the cover and snap lid securely shut. Pull each wipe with a little force. To keep wipes fresh and moist, close lid after use.

Wipe your hands thoroughly and let dry. Let hands completely dry before coming in close contact with any open flame.

For best results, clean excessively dirty areas before using wipes.

Please do not flush these wipes. We recommend that you dispose of them in the trash. Flushing wipes can cause damaged in plumbing.